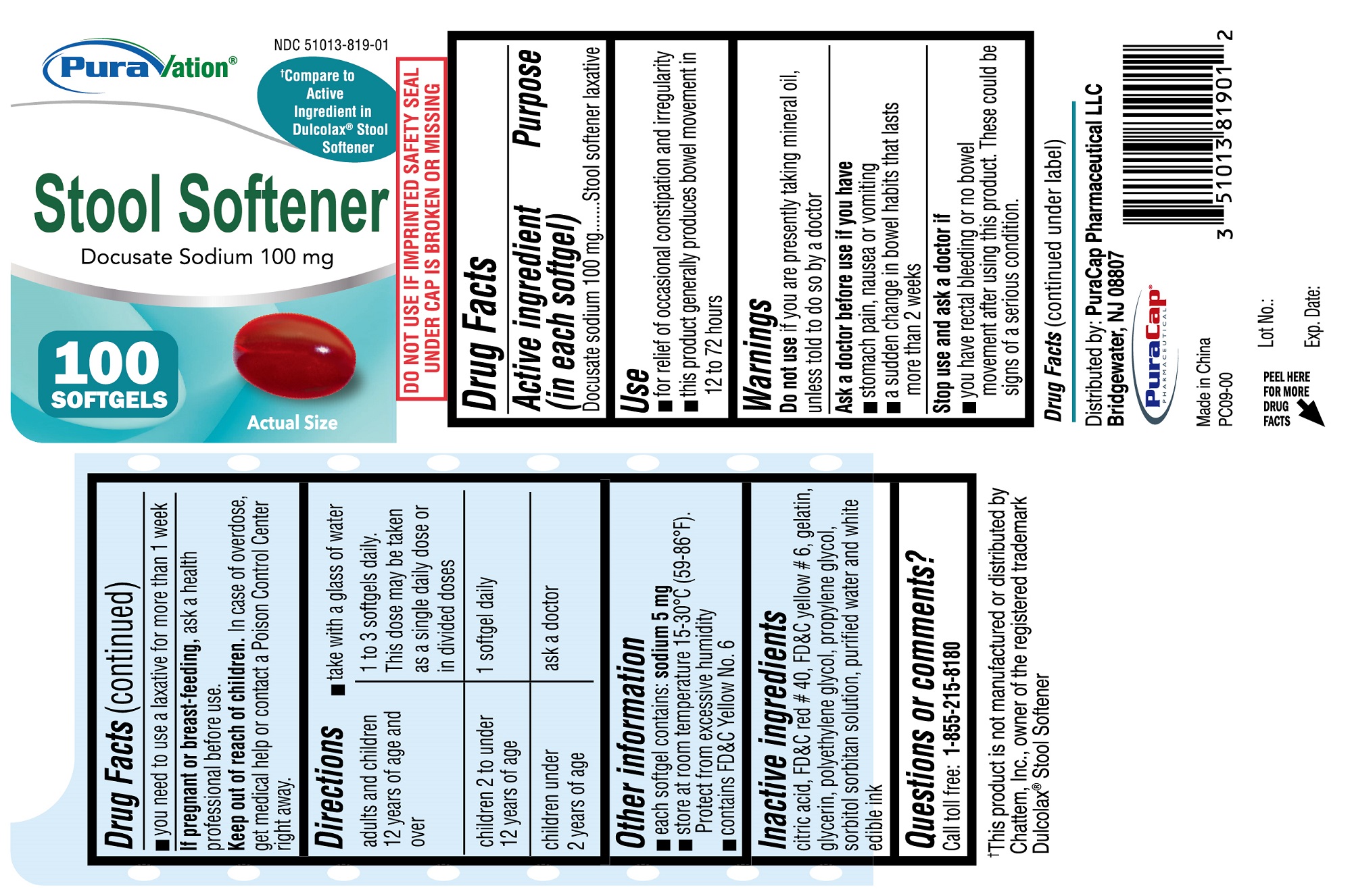 DRUG LABEL: Stool Softener
NDC: 51013-819 | Form: CAPSULE, LIQUID FILLED
Manufacturer: PuraCap Pharmaceutical LLC
Category: otc | Type: HUMAN OTC DRUG LABEL
Date: 20241118

ACTIVE INGREDIENTS: DOCUSATE SODIUM 100 mg/1 1
INACTIVE INGREDIENTS: GELATIN, UNSPECIFIED; PROPYLENE GLYCOL; SORBITOL; FD&C RED NO. 40; WATER; ANHYDROUS CITRIC ACID; POLYETHYLENE GLYCOL, UNSPECIFIED; FD&C YELLOW NO. 6; GLYCERIN

Docusate Sodium 100 mg

Drug Facts

Active ingredient (in each softgel)

Docusate Sodium 100 mg

Purpose

Stool softener laxative

Use

- for relief of occasional constipation and irregularity.
- This product generally produces bowel movement in 12 to 72 hours.

Warnings

Do not use if you are presently taking mineral oil, unless told to do so by a doctor

Ask a doctor before use if you have

- stomach pain, nausea or vomiting
- a sudden change in bowel habits that lasts more than 2 weeks

Stop use and ask a doctor if

- you have rectal bleeding or no bowel movement after using this product. These could be signs of a serious condition.
- you need to use a laxative for more than 1 week.

PREGNANCY OR BREAST FEEDING

If pregnant or breast-feeding, ask a health professional before use.

Keep out of reach of children.

Overdose warning

In case of overdose, get medical help or contact a Posion Control Center right away.

Directions

- take with a glass of water -see Overdose warning

adults and children 12 years; of age and over | 1 to 3 softgels daily. This dose may be taken as a single daily dose; or in divided doses
children 2 to under 12 years of age | 1 softgel daily
children under 2 years of age | ask a doctor

Other information

- each softgel contains: sodium 5mg
- store at room temperature 15°-30° C (59°-86° F). Protect from excessive humidity
- contains FD&C Yellow No. 6

Inactive Ingredients

citric acid, FD&C red #40, FD&C yellow #6, gelatin, glycerin, polyethylene glycol, propylene glycol, sorbitol sorbitan solution, purified water and white edible ink

Questions or comments?

Call toll free: 1-855-215-8180

PACKAGE LABEL

PuraVation Stool Softener

Docusate Sodium - 100 mg EACH

100 SOFTGELS

NDC 51013-819-01